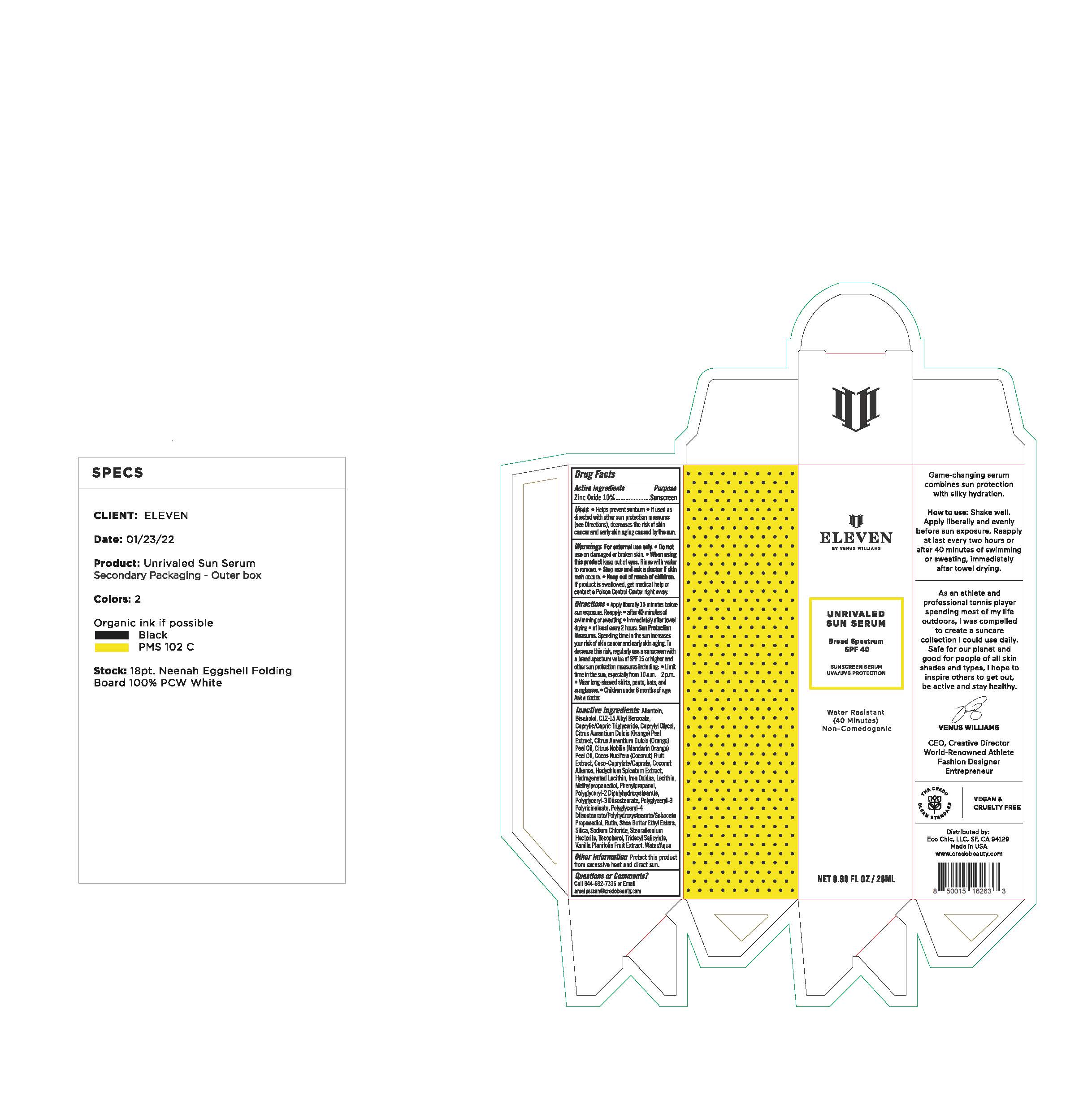 DRUG LABEL: ELEVEN UNRIVALED SERUM
NDC: 79163-399 | Form: LOTION
Manufacturer: Eco Chic, LLC
Category: otc | Type: HUMAN OTC DRUG LABEL
Date: 20251016

ACTIVE INGREDIENTS: ZINC OXIDE 110 mg/1 mL
INACTIVE INGREDIENTS: PHENYLPROPANOL; LECITHIN, SOYBEAN; METHYLPROPANEDIOL; POLYGLYCERYL-2 DIPOLYHYDROXYSTEARATE; ALLANTOIN; ALKYL (C12-15) BENZOATE; .ALPHA.-BISABOLOL, (+)-; WATER; SODIUM CHLORIDE; HYDROGENATED SOYBEAN LECITHIN; VANILLA PLANIFOLIA WHOLE; POLYGLYCERYL-3 RICINOLEATE; POLYGLYCERYL-4 DIISOSTEARATE/POLYHYDROXYSTEARATE/SEBACATE; COCOS NUCIFERA WHOLE; HEDYCHIUM SPICATUM WHOLE; SHEA BUTTER ETHYL ESTERS; PROPANEDIOL; CITRUS NOBILIS; TRIDECYL SALICYLATE; STEARALKONIUM HECTORITE; POLYGLYCERYL-3 DIISOSTEARATE; CITRUS AURANTIUM FRUIT OIL; COCONUT ALKANES; RUTIN; FERRIC OXIDE YELLOW; SILICON DIOXIDE; TOCOPHEROL; CAPRYLYL GLYCOL; COCO-CAPRYLATE

ELEVEN UNRIVALED SERUM